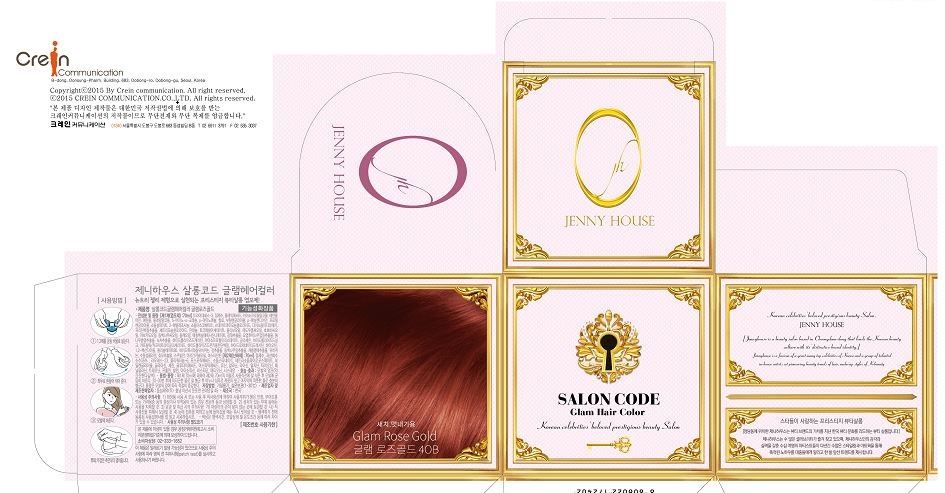 DRUG LABEL: SALON CODE Glam Hair Color Glam Rose Gold
NDC: 70778-0011 | Form: KIT | Route: TOPICAL
Manufacturer: Daolcosmetic Co.,ltd
Category: otc | Type: HUMAN OTC DRUG LABEL
Date: 20180910

ACTIVE INGREDIENTS: P-AMINOPHENOL 0.8 g/100 mL; HYDROGEN PEROXIDE 5.845 g/100 mL
INACTIVE INGREDIENTS: WATER; WATER

Drug Facts

ACTIVE INGREDIENT

p-Aminophenol

INACTIVE INGREDIENT

ethanolamine, alcohol, butylene glycol, sodium sulfite, etc

PURPOSE

hair coloring

Keep out or reach of the children

INDICATIONS AND USAGE

First, wear gloves before starting the coloring session. Pour an equal amount of #1(colorant) & #2(developer) into the provided plastic container and close the cap until you hear the click sound. Mix well by shaking the container horizontally or sideways until the mixture turns to gel. (Do NOT shake the container vertically or up & down). Carefully open the container from the side and scoop the contents on hand to start the procedure. Use appropriate amounts as you color by sections to apply the gel to the top, sides, and the back. Gently rub the gel against hair. With the remaining gel, lightly apply along the hairline to finish the procedure. Wait according to the indicated time for the color to process (20min. to cover gray hair). After the desired color is obtained, wash and rinse several times with lukewarm water until water runs clear. NOTE: Leave extra 10 min. for thick hair and/or if the coloring procedure is done at cool temperature (below room temperature).

WARNINGS

For external use only.

This product contains ingredients which may cause skin irritation on certain individuals and a preliminary test should first be made. This product must not be used for dyeing of eyelashes or eyebrows. If you were to do so, it may cause blindness. When product comes in contact with eyes during the coloring session, rinse immediately with cool, running water and consult a physician immediately. Keep out of reach of children. If swallowed, get medical help or contact a Poison Control Center right away. Processed color may be different from the color chart indicated on the box due to condition of individual, hair, and/or temperature. Before coloring, please read the instructions thoroughly.

DOSAGE AND ADMINISTRATION

For external use only